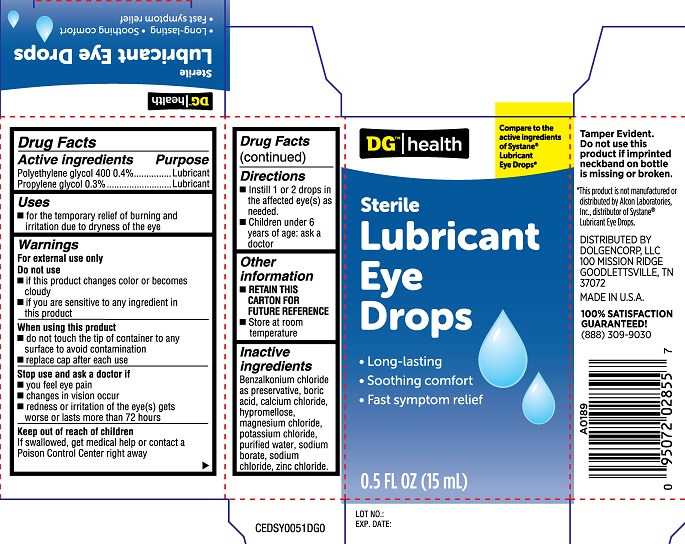 DRUG LABEL: DG Lubricant Eye Drops
NDC: 55910-364 | Form: SOLUTION
Manufacturer: Dolgencorp LLC
Category: otc | Type: HUMAN OTC DRUG LABEL
Date: 20251230

ACTIVE INGREDIENTS: POLYETHYLENE GLYCOL 400 0.4 g/100 mL; PROPYLENE GLYCOL 0.3 g/100 mL
INACTIVE INGREDIENTS: CALCIUM CHLORIDE; HYPROMELLOSE, UNSPECIFIED; SODIUM BORATE; BORIC ACID; POTASSIUM CHLORIDE; BENZALKONIUM CHLORIDE; ZINC CHLORIDE; MAGNESIUM CHLORIDE; WATER; SODIUM CHLORIDE

DG Lubricant Eye Drops (PLD)

Active ingredients

Polyethylene glycol 400 0.4%

Propylene glycol 0.3%

PURPOSE

Active ingredients

Polyethylene glycol .....Lubricant

Propylene glycol.....Lubricant

Uses

- for the temporary relief of burning and irritation due to dryness of the eye

WARNINGS

Warnngs

For external use only

Do not use

- if this product changes color or becomes cloudy
- if you are sensitive to any ingredient in this product

When using this product

- do not touch the tip of container to any surface to avoid contamination
- replace cap after each use

Stop use and ask a doctor if

- you feel eye pain
- changes in vision occur
- redness or irritation of the eye(s) gets worse or lasts more than 72 hours

Keep out of reach of children

If swallowed, get medical help or contact a Poison Control Center right away

Directions

- Instill 1 or 2 drops in the affected eye(s) as needed
- Children under 6 years of age: ask a doctor

Other information

- RETAIN THIS CARTON FOR FUTURE REFERENCE
- Store at room temperature

Inactive ingredients

Benzalkonium chloride as preservative, boric acid, calcium chloride, hypromellose, magnesium chloride, potassium chloride, purified water, sodium borate, sodium chloride, zinc chloride